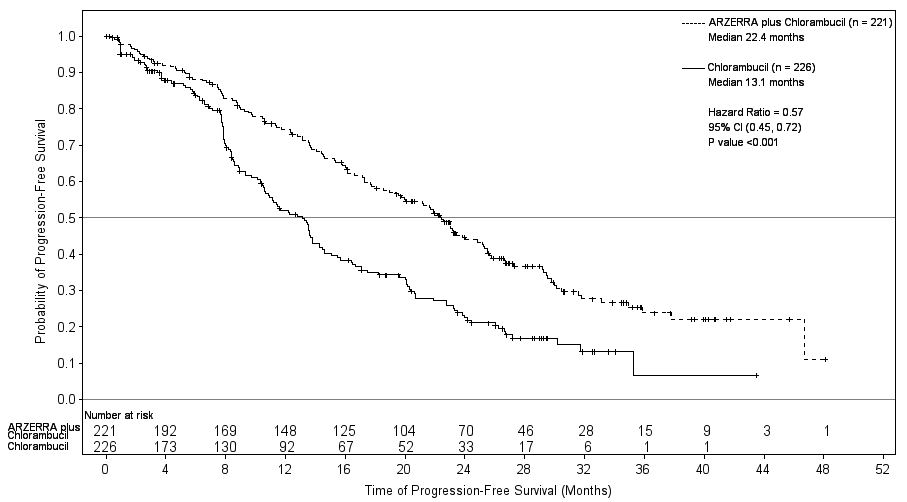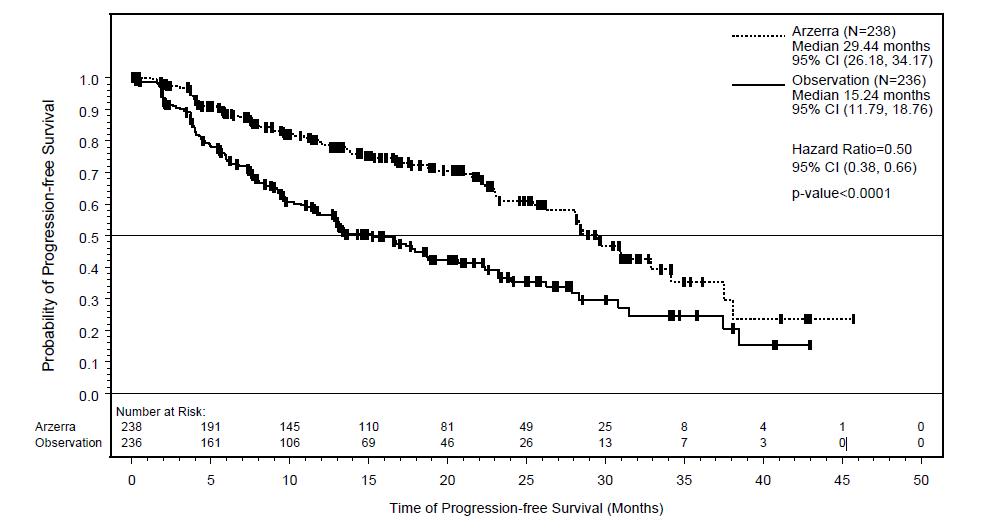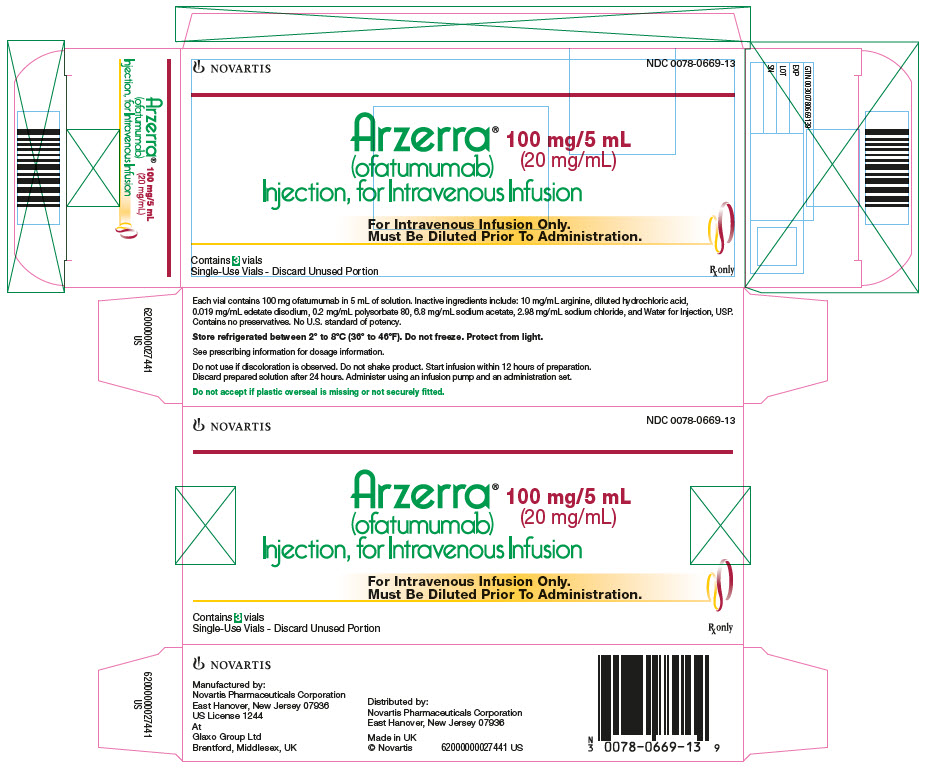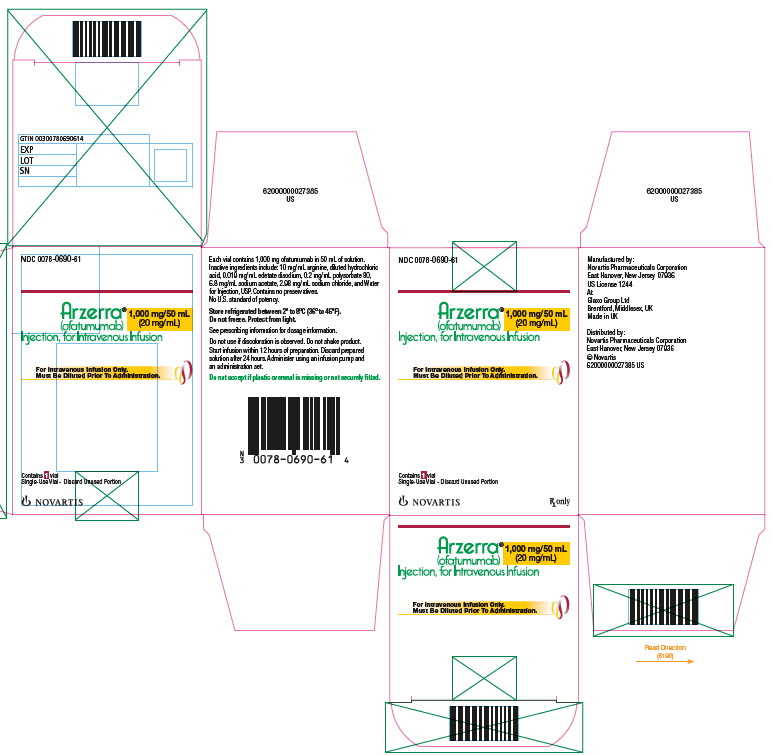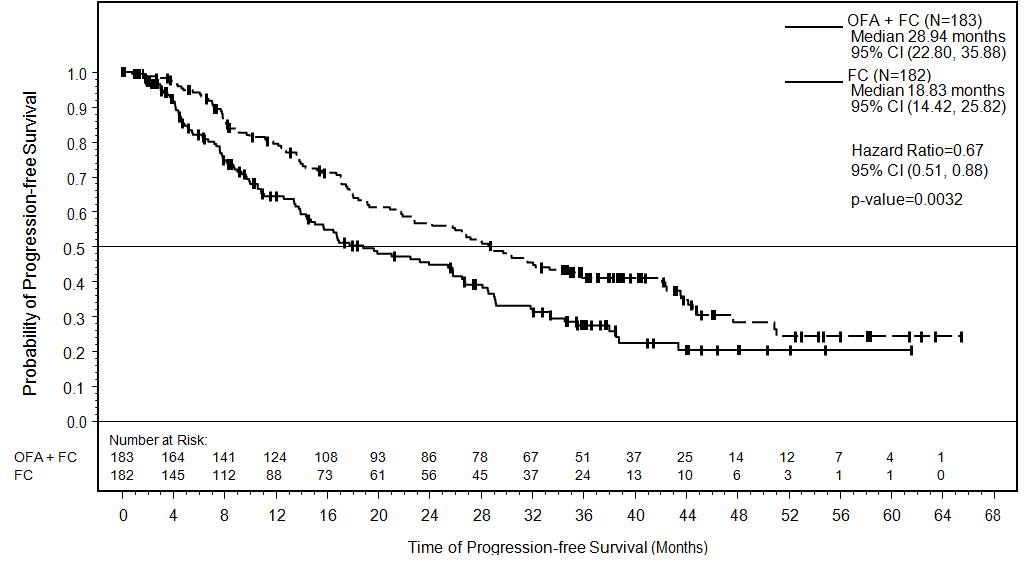 DRUG LABEL: ARZERRA
NDC: 0078-0669 | Form: INJECTION, SOLUTION
Manufacturer: Novartis Pharmaceuticals Corporation
Category: prescription | Type: HUMAN PRESCRIPTION DRUG LABEL
Date: 20260217

ACTIVE INGREDIENTS: OFATUMUMAB 20 mg/1 mL
INACTIVE INGREDIENTS: ARGININE; HYDROCHLORIC ACID; EDETATE DISODIUM; POLYSORBATE 80; SODIUM ACETATE; SODIUM CHLORIDE; WATER

HIGHLIGHTS OF PRESCRIBING INFORMATION

These highlights do not include all the information needed to use ARZERRA safely and effectively. See full prescribing information for ARZERRA.
ARZERRA® (ofatumumab) injection, for intravenous use
Initial U.S. Approval: 2009

RECENT MAJOR CHANGES

Indications and Usage, Extended Treatment in CLL (1) | 1/2016
Indications and Usage, Relapsed CLL (1) | 8/2016
Dosage and Administration, Recommended Dosage Regimen (2.1) | 1/2016
Dosage and Administration, Administration (2.2) | 8/2016
Dosage and Administration, Pre-medication (2.4) | 1/2016

WARNING: HEPATITIS B VIRUS REACTIVATION AND PROGRESSIVE MULTIFOCAL LEUKOENCEPHALOPATHY

See full prescribing information for complete boxed warning.

- Hepatitis B Virus (HBV) reactivation, in some cases resulting in fulminant hepatitis, hepatic failure, and death. (5.2)
- Progressive Multifocal Leukoencephalopathy (PML) resulting in death. (5.4)

1 INDICATIONS AND USAGE

ARZERRA (ofatumumab) is a CD20-directed cytolytic monoclonal antibody indicated for the treatment of chronic lymphocytic leukemia (CLL) (1):

- in combination with chlorambucil, for the treatment of previously untreated patients with CLL for whom fludarabine-based therapy is considered inappropriate.
- in combination with fludarabine and cyclophosphamide for the treatment of patients with relapsed CLL.
- for extended treatment of patients who are in complete or partial response after at least two lines of therapy for recurrent or progressive CLL.
- for the treatment of patients with CLL refractory to fludarabine and alemtuzumab.

2 DOSAGE AND ADMINISTRATION

- Dilute and administer as an intravenous infusion. Do not administer subcutaneously or as an intravenous push or bolus. (2.1)
- Previously untreated CLL in combination with chlorambucil recommended dosage and schedule is:
  - 300 mg on Day 1 followed by 1,000 mg on Day 8 (Cycle 1)
  - 1,000 mg on Day 1 of subsequent 28-day cycles for a minimum of 3 cycles until best response or a maximum of 12 cycles. (2.1)
- Relapsed CLL in combination with fludarabine and cyclophosphamide recommended dosage and schedule is:
  - 300 mg on Day 1 followed by 1,000 mg on Day 8 (Cycle 1)
  - 1,000 mg on Day 1 of subsequent 28-day cycles for a maximum of 6 cycles (2.1)
- Extended treatment in CLL recommended dosage and schedule is:
  - 300 mg on Day 1 followed by
  - 1,000 mg 1 week later on Day 8, followed by
  - 1,000 mg 7 weeks later and every 8 weeks thereafter for up to a maximum of 2 years. (2.1)
- Refractory CLL recommended dosage and schedule is:
  - 300 mg initial dose, followed 1 week later by
  - 2,000 mg weekly for 7 doses, followed 4 weeks later by
  - 2,000 mg every 4 weeks for 4 doses. (2.1)
- Administer where facilities to adequately monitor and treat infusion reactions are available. (2.2)
- Pre-medicate with acetaminophen, antihistamine, and corticosteroid. (2.4)

3 DOSAGE FORMS AND STRENGTHS

- 100 mg/5 mL single-use vial for intravenous infusion. (3)
- 1,000 mg/50 mL single-use vial for intravenous infusion. (3)

4 CONTRAINDICATIONS

None. (4)

5 WARNINGS AND PRECAUTIONS

- Infusion Reactions: Pre-medicate with corticosteroid, acetaminophen, and an antihistamine. Monitor patients during infusions. Interrupt infusion if infusion reactions occur. (2.3, 2.4, 5.1)
- Tumor Lysis Syndrome: Anticipate TLS in high-risk patients; pre-medicate with anti-hyperuricemics and hydration. (5.5)
- Cytopenias: Neutropenia, anemia, and thrombocytopenia occur. Late-onset and prolonged neutropenia can also occur. Monitor complete blood counts at regular intervals. (5.6)

6 ADVERSE REACTIONS

- Previously Untreated CLL: Common adverse reactions (≥10%) were infusion reactions and neutropenia. (6)
- Relapsed CLL: Common adverse reactions (>10%) were infusion reactions, neutropenia, leukopenia and febrile neutropenia. (6)
- Extended Treatment in CLL: Common adverse reactions (≥10%) were infusion reactions, neutropenia, and upper respiratory tract infection. (6)
- Refractory CLL: Common adverse reactions (≥10%) were neutropenia, pneumonia, pyrexia, cough, diarrhea, anemia, fatigue, dyspnea, rash, nausea, bronchitis, and upper respiratory tract infections. (6)

To report SUSPECTED ADVERSE REACTIONS, contact Novartis Pharmaceuticals Corporation at 1-888-669-6682 or FDA at 1-800-FDA-1088 or www.fda.gov/medwatch.

8 USE IN SPECIFIC POPULATIONS

- Pregnancy: May cause fetal B-cell depletion. (8.1)

FULL PRESCRIBING INFORMATION

WARNING: HEPATITIS B VIRUS REACTIVATION AND PROGRESSIVE MULTIFOCAL LEUKOENCEPHALOPATHY

- Hepatitis B Virus (HBV) reactivation can occur in patients receiving CD20-directed cytolytic antibodies, including ARZERRA®, in some cases resulting in fulminant hepatitis, hepatic failure, and death [see Warnings and Precautions (5.2)].
- Progressive Multifocal Leukoencephalopathy (PML) resulting in death can occur in patients receiving CD20-directed cytolytic antibodies, including ARZERRA [see Warnings and Precautions (5.4)].

1 INDICATIONS AND USAGE

Chronic Lymphocytic Leukemia (CLL)

ARZERRA (ofatumumab) is indicated:

- in combination with chlorambucil, for the treatment of previously untreated patients with CLL for whom fludarabine-based therapy is considered inappropriate [see Clinical Studies (14.1)]
- in combination with fludarabine and cyclophosphamide for the treatment of patients with relapsed CLL [see Clinical Studies (14.2)]
- for extended treatment of patients who are in complete or partial response after at least two lines of therapy for recurrent or progressive CLL [see Clinical Studies (14.3)]
- for the treatment of patients with CLL refractory to fludarabine and alemtuzumab [see Clinical Studies (14.4)]

2 DOSAGE AND ADMINISTRATION

2.1 Recommended Dosage Regimen

- Dilute and administer as an intravenous infusion according to the following schedules.
- Do not administer as an intravenous push or bolus or as a subcutaneous injection.
- Pre-medicate before each infusion [see Dosage and Administration (2.4)].

Previously Untreated CLL:

The recommended dosage and schedule in combination with chlorambucil is:

- 300 mg on Day 1, followed 1 week later by 1,000 mg on Day 8 (Cycle 1), followed by
- 1,000 mg on Day 1 of subsequent 28-day cycles for a minimum of 3 cycles until best response or a maximum of 12 cycles.

Relapsed CLL:

The recommended dosage and schedule in combination with fludarabine and cyclophosphamide is:

- 300 mg on Day 1, followed 1 week later by 1,000 mg on Day 8 (Cycle 1), followed by
- 1,000 mg on Day 1 of subsequent 28-day cycles for a maximum of 6 cycles.

Extended Treatment in CLL: The recommended dosage and schedule as single-agent extended treatment in CLL is:

- 300 mg on Day 1, followed by
- 1,000 mg 1 week later on Day 8, followed by
- 1,000 mg 7 weeks later and every 8 weeks thereafter for up to a maximum of 2 years.

Refractory CLL: The recommended dosage and schedule is 12 doses administered as follows:

- 300 mg initial dose on Day 1, followed 1 week later by
- 2,000 mg weekly for 7 doses (Infusions 2 through 8), followed 4 weeks later by
- 2,000 mg every 4 weeks for 4 doses (Infusions 9 through 12).

2.2 Administration

Administer ARZERRA in an environment where facilities to adequately monitor and treat infusion reactions are available [see Warnings and Precautions (5.1)].

Prepare all doses in 1,000 mL of 0.9% Sodium Chloride Injection, USP [see Dosage and Administration (2.5)].

Previously Untreated CLL, Relapsed CLL, and Extended Treatment in CLL:

- For initial 300-mg dose: Initiate infusion at a rate of 3.6 mg/hour (12 mL/hour).
- For subsequent infusions of 1,000 mg: Initiate infusion at a rate of 25 mg/hour (25 mL/hour). Initiate infusion at a rate of 12 mg/hour if a Grade 3 or greater infusion-related adverse event was experienced during the previous infusion.

In the absence of an infusion-related adverse event, the rate of infusion may be increased every 30 minutes (Table 1). Do not exceed the infusion rates in Table 1.

Table 1. Infusion Rates for ARZERRA in Previously Untreated CLL, Relapsed CLL, and Extended Treatment in CLL
Interval After; Start of Infusion (min) | Initial 300 mg Dosea; (mL/hour) | Subsequent Infusionsb; (mL/hour)
0-30 | 12 | 25
31-60 | 25 | 50
61-90 | 50 | 100
91-120 | 100 | 200
121-150 | 200 | 400
151-180 | 300 | 400
>180 | 400 | 400
a Initial 300 mg: median durations of infusions = 4.8 to 5.2 hours.
b Subsequent infusions of 1,000 mg: median durations of infusions = 4.2 to 4.4 hours.

Refractory CLL:

- Infusion 1 (300-mg dose): Initiate infusion at a rate of 3.6 mg/hour (12 mL/hour).
- Infusion 2 (2,000-mg dose): Initiate infusion at a rate of 24 mg/hour (12 mL/hour).
- Infusions 3 through 12 (2,000-mg doses): Initiate infusion at a rate of 50 mg/hour (25 mL/hour).

In the absence of an infusion-related adverse event, the rate of infusion may be increased every 30 minutes (Table 2). Do not exceed the infusion rates in Table 2.

Table 2. Infusion Rates for ARZERRA in Refractory CLL
Interval after Start of Infusion (min) | Infusions 1 and 2a; (mL/hour) | Subsequent Infusions b; (mL/hour)
0-30 | 12 | 25
31-60 | 25 | 50
61-90 | 50 | 100
91-120 | 100 | 200
>120 | 200 | 400
a Infusions 1 and 2 (300 mg and 2,000 mg): median duration of infusions = 6.8 hours.
b Subsequent infusions of 2,000 mg: median durations of infusions = 4.2 to 4.4 hours.

2.3 Infusion Rate Dose Modification for Infusion Reactions

- Interrupt infusion for infusion reactions of any severity [see Warnings and Precautions (5.1)]. Treatment can be resumed at the discretion of the treating physician. The following infusion rate modifications can be used as a guide.
- If the infusion reaction resolves or remains less than or equal to Grade 2, resume infusion with the following modifications according to the initial Grade of the infusion reaction.
  - Grade 1 or 2: Infuse at one‑half of the previous infusion rate.
  - Grade 3 or 4: Infuse at a rate of 12 mL/hour.
- After resuming the infusion, the infusion rate may be increased according to Tables 1 and 2 above, based on patient tolerance.
- Consider permanent discontinuation of ARZERRA if the severity of the infusion reaction does not resolve to less than or equal to Grade 2 despite adequate clinical intervention.
- Permanently discontinue therapy for patients who develop an anaphylactic reaction to ARZERRA.

2.4 Premedication

Patients should receive all of the following premedication agents 30 minutes to 2 hours prior to each infusion of ARZERRA. See Table 3 for pre-medication schedule prior to each infusion.

Table 3. Premedication Schedule for ARZERRA
 | Previously Untreated CLL, Relapsed CLL or Extended Treatment in CLL |  | Refractory CLL
Infusion Number | 1 and 2 | 3 and beyonda | 1, 2, and 9 | 3 to 8 | 10 to 12
Intravenous corticosteroid (prednisolone or equivalent) | 50 mg | 0-50 mgb | 100 mg | 0-100 mgb | 50-100 mgc
Oral acetaminophen | 1,000 mg
Oral or intravenous antihistamine | Diphenhydramine 50 mg or cetirizine 10 mg (or equivalent)
a Up to 13 infusions in previously untreated CLL; up to 7 infusions in relapsed CLL, up to 14 infusions in extended treatment in CLL.
b Corticosteroid may be reduced or omitted for subsequent infusions if a Grade 3 or greater infusion-related adverse event did not occur with the preceding infusion(s).
c Prednisolone may be given at reduced dose of 50 mg to 100 mg (or equivalent) if a Grade 3 or greater infusion-related adverse event did not occur with Infusion 9.

2.5 Preparation and Administration

- Do not shake product.
- Inspect parenteral drug products visually for particulate matter and discoloration prior to administration. ARZERRA should be a clear to opalescent, colorless solution. The solution should not be used if discolored or cloudy, or if foreign particulate matter is present.

Preparation of Solution:

- 300-mg dose: Withdraw and discard 15 mL from a 1,000-mL bag of 0.9% Sodium Chloride Injection, USP. Withdraw 5 mL from each of 3 single-use 100-mg vials of ARZERRA and add to the bag. Mix diluted solution by gentle inversion.
- 1,000-mg dose: Withdraw and discard 50 mL from a 1,000-mL bag of 0.9% Sodium Chloride Injection, USP. Withdraw 50 mL from 1 single-use 1,000-mg vial of ARZERRA and add to the bag. Mix diluted solution by gentle inversion.
- 2,000-mg dose: Withdraw and discard 100 mL from a 1,000-mL bag of 0.9% Sodium Chloride Injection, USP. Withdraw 50 mL from each of 2 single-use 1,000-mg vials of ARZERRA and add to the bag. Mix diluted solution by gentle inversion.
- Store diluted solution between 2° to 8°C (36° to 46°F).
- No incompatibilities between ARZERRA and polyvinylchloride or polyolefin bags and administration sets have been observed.

Administration Instructions:

- Do not mix ARZERRA with, or administer as an infusion with other medicinal products.
- Administer using an infusion pump and an administration set.
- Flush the intravenous line with 0.9% Sodium Chloride Injection, USP before and after each dose.
- Start infusion within 12 hours of preparation.
- Discard prepared solution after 24 hours.

3 DOSAGE FORMS AND STRENGTHS

- 100 mg/5 mL single‑use vial for intravenous infusion.
- 1,000 mg/50 mL single‑use vial for intravenous infusion.

4 CONTRAINDICATIONS

None.

5 WARNINGS AND PRECAUTIONS

5.1 Infusion Reactions

ARZERRA can cause serious, including fatal, infusion reactions manifesting as bronchospasm, dyspnea, laryngeal edema, pulmonary edema, flushing, hypertension, hypotension, syncope, cardiac events (e.g., myocardial ischemia/infarction, acute coronary syndrome, arrhythmia, bradycardia), back pain, abdominal pain, pyrexia, rash, urticaria, angioedema, cytokine release syndrome, and anaphylactoid/anaphylactic reactions. Infusion reactions occur more frequently with the first 2 infusions. These reactions may result in temporary interruption or withdrawal of treatment [see Adverse Reactions (6.1)].

Pre-medicate with acetaminophen, an antihistamine, and a corticosteroid [see Dosage and Administration (2.1, 2.4)]. Infusion reactions may occur despite premedication. Interrupt infusion with ARZERRA for infusion reactions of any severity. Institute medical management for severe infusion reactions including angina or other signs and symptoms of myocardial ischemia [see Dosage and Administration (2.3)]. If an anaphylactic reaction occurs, immediately and permanently discontinue ARZERRA and initiate appropriate medical treatment.

5.2 Hepatitis B Virus Reactivation

Hepatitis B virus (HBV) reactivation, in some cases resulting in fulminant hepatitis, hepatic failure, and death, has occurred in patients treated with ARZERRA. Cases have been reported in patients who are hepatitis B surface antigen (HBsAg) positive and also in patients who are HBsAg negative but are hepatitis B core antibody (anti-HBc) positive. Reactivation also has occurred in patients who appear to have resolved hepatitis B infection (i.e., HBsAg negative, anti-HBc positive, and hepatitis B surface antibody [anti-HBs] positive).

HBV reactivation is defined as an abrupt increase in HBV replication manifesting as a rapid increase in serum HBV DNA level or detection of HBsAg in a person who was previously HBsAg negative and anti-HBc positive. Reactivation of HBV replication is often followed by hepatitis, i.e., increase in transaminase levels and, in severe cases, increase in bilirubin levels, liver failure, and death.

Screen all patients for HBV infection by measuring HBsAg and anti-HBc before initiating treatment with ARZERRA. For patients who show evidence of hepatitis B infection (HBsAg positive [regardless of antibody status] or HBsAg negative but anti-HBc positive), consult physicians with expertise in managing hepatitis B regarding monitoring and consideration for HBV antiviral therapy.

Monitor patients with evidence of current or prior HBV infection for clinical and laboratory signs of hepatitis or HBV reactivation during and for several months following treatment with ARZERRA. HBV reactivation has been reported for at least 12 months following completion of therapy.

In patients who develop reactivation of HBV while receiving ARZERRA, immediately discontinue ARZERRA and any concomitant chemotherapy, and institute appropriate treatment. Resumption of ARZERRA in patients whose HBV reactivation resolves should be discussed with physicians with expertise in managing hepatitis B. Insufficient data exist regarding the safety of resuming ARZERRA in patients who develop HBV reactivation.

5.3 Hepatitis B Virus Infection

Fatal infection due to hepatitis B in patients who have not been previously infected has been observed with ARZERRA. Monitor patients for clinical and laboratory signs of hepatitis.

5.4 Progressive Multifocal Leukoencephalopathy

Progressive multifocal leukoencephalopathy (PML) resulting in death has occurred with ARZERRA. Consider PML in any patient with new onset of or changes in pre-existing neurological signs or symptoms. If PML is suspected, discontinue ARZERRA and initiate evaluation for PML including neurology consultation.

5.5 Tumor Lysis Syndrome

Tumor lysis syndrome (TLS), including the need for hospitalization, has occurred in patients treated with ARZERRA. Patients with high tumor burden and/or high circulating lymphocyte counts (>25 x 10^9/L) are at greater risk for developing TLS. Consider tumor lysis prophylaxis with anti-hyperuricemics and hydration beginning 12 to 24 hours prior to infusion of ARZERRA. For treatment of TLS, administer aggressive intravenous hydration and anti-hyperuricemic agents, correct electrolyte abnormalities, and monitor renal function.

5.6 Cytopenias

Severe cytopenias, including neutropenia, thrombocytopenia, and anemia, can occur with ARZERRA. Pancytopenia, agranulocytosis, and fatal neutropenic sepsis have occurred in patients who received ARZERRA in combination with chlorambucil. Grade 3 or 4 late-onset neutropenia (onset at least 42 days after last treatment dose) and/or prolonged neutropenia (not resolved between 24 and 42 days after last treatment dose) were reported in patients who received ARZERRA [see Adverse Reactions (6.1)]. Monitor complete blood counts at regular intervals during and after conclusion of therapy, and increase the frequency of monitoring in patients who develop Grade 3 or 4 cytopenias.

5.7 Immunizations

The safety of immunization with live viral vaccines during or following administration of ARZERRA has not been studied. Do not administer live viral vaccines to patients who have recently received ARZERRA. The ability to generate an immune response to any vaccine following administration of ARZERRA has not been studied.

6 ADVERSE REACTIONS

The following serious adverse reactions are discussed in greater detail in other sections of the labeling:

- Infusion Reactions [see Warnings and Precautions (5.1)]
- Hepatitis B Virus Reactivation [see Warnings and Precautions (5.2)]
- Hepatitis B Virus Infection [see Warnings and Precautions (5.3)]
- Progressive Multifocal Leukoencephalopathy [see Warnings and Precautions (5.4)]
- Tumor Lysis Syndrome [see Warnings and Precautions (5.5)]
- Cytopenias [see Warnings and Precautions (5.6)]

6.1 Clinical Trials Experience

Because clinical trials are conducted under widely varying conditions, adverse reaction rates observed in the clinical trials of a drug cannot be directly compared with rates in the clinical trials of another drug and may not reflect the rates observed in practice.

Previously Untreated CLL: The safety of ARZERRA was evaluated in an open-label, parallel-arm, randomized trial (Study 1) in 444 patients with previously untreated CLL. Patients were randomized to receive either ARZERRA as an intravenous infusion every 28 days in combination with chlorambucil (n = 217) or chlorambucil as a single agent (n = 227). In both arms, patients received chlorambucil 10 mg/m^2 orally on Days 1 to 7 every 28 days. The infusion schedule for ARZERRA was 300 mg administered on Cycle 1 Day 1, 1,000 mg administered on Cycle 1 Day 8, and 1,000 mg administered on Day 1 of subsequent 28-day cycles. The median number of cycles of ARZERRA completed was 6.

The most common adverse reactions (≥10%) were infusion reactions and neutropenia (Table 4).

The data described in Table 4 include relevant adverse reactions occurring up to 60 days after the last dose of study medication; Table 5 includes relevant hematologic laboratory abnormalities.

Table 4. Adverse Reactions with ≥5% Incidence in Patients Receiving ARZERRA plus Chlorambucil and Also ≥2% More than Patients Receiving Chlorambucil
Adverse Reactions | ARZERRA plus Chlorambucil; (N = 217) |  | Chlorambucil; (N = 227)
Adverse Reactions | All Grades; % | Grade ≥3; % | All Grades; % | Grade ≥3; %
Infusion reactionsa | 67 | 10 | 0 | 0
Neutropenia | 27 | 26 | 18 | 14
Asthenia | 8 | <1 | 5 | 0
Headache | 7 | <1 | 3 | 0
Leukopenia | 6 | 3 | 2 | <1
Herpes simplexb | 6 | 0 | 4 | <1
Lower respiratory tract infection | 5 | 1 | 3 | <1
Arthralgia | 5 | <1 | 3 | 0
Upper abdominal pain | 5 | 0 | 3 | 0
a Includes events which occurred on the day of an infusion or within 24 hours of the end of an infusion and resulted in an interruption or discontinuation of treatment. Infusion reactions may include, but are not limited to, chills, dyspnea, flushing, hypotension, nausea, pain, pruritus, pyrexia, rash, and urticaria.
b Includes oral herpes, herpes, herpes virus infection, genital herpes, and herpes simplex.

Table 5. Post-baseline Hematologic Laboratory Abnormalities Occurring with ≥5% Incidence in Patients Receiving ARZERRA plus Chlorambucil and Also ≥2% More than Patients Receiving Chlorambucil
Investigations | ARZERRA plus Chlorambucil; (N = 217) |  | Chlorambucil; (N = 227)
Investigations | All Grades; % | Grade ≥3; % | All Grades; % | Grade ≥3; %
Leukopenia | 67 | 23 | 28 | 4
Neutropenia | 66 | 29 | 56 | 24
Lymphopenia | 52 | 29 | 20 | 7

Infusion Reactions: Overall, 67% of patients who received ARZERRA in combination with chlorambucil experienced one or more symptoms of infusion reactions (10% were Grade 3 or greater; none were fatal). Infusion reactions occurred most frequently during Cycle 1 (56% on Day 1 [6% were Grade 3 or greater] and 23% on Day 8 [3% were Grade 3 or greater]) and decreased with subsequent infusions. Infusion reactions led to discontinuation of treatment in 3% of patients. Serious adverse events of infusion reactions occurred in 2% of patients.

Neutropenia: Overall, 3% of patients had neutropenia as a serious adverse event, reported up to 60 days after the last dose. One patient died with neutropenic sepsis and agranulocytosis. Prolonged neutropenia occurred in 6% of patients receiving ARZERRA in combination with chlorambucil compared with 4% of patients receiving chlorambucil. Late-onset neutropenia occurred in 6% of patients receiving ARZERRA in combination with chlorambucil compared with 1% of patients receiving chlorambucil alone.

Relapsed CLL: The safety of ARZERRA in combination with fludarabine and cyclophosphamide compared with fludarabine and cyclophosphamide was evaluated in a randomized, open-label, parallel-arm, multicenter trial (Study 2) in 359 patients with relapsed CLL. Patients were randomized to receive ARZERRA as an intravenous infusion (Cycle 1: 300 mg on Day 1 and 1,000 mg on Day 8; followed by 1,000 mg on Day 1 of subsequent 28-day cycles for a maximum of 6 cycles). Standard fludarabine and cyclophosphamide therapy was administered as a 3-day course starting on the first day of each cycle, with initial dosages of 25 mg/m^2 for fludarabine and 250 mg/m^2 for cyclophosphamide. Table 6 includes adverse reactions occurring up to 60 days after the last dose of study medication.

The most common adverse reactions (≥10%) were infusion reactions, neutropenia, leukopenia and febrile neutropenia (Table 6).

Table 6. Adverse Reactions with ≥5% Incidence in Patients Receiving ARZERRA plus FC and Also ≥2% More than in Patients in Fludarabine and Cyclophosphamide Arm
Adverse Reactions | ARZERRA plus Fludarabine and Cyclophosphamide; (N = 181) |  | Fludarabine and Cyclophosphamide Arm; (N = 178)
Adverse Reactions | All Grades; % | Grade >3; % | All Grades; % | Grade >3; %
Infusion reactionsa | 60 | 9 | 28 | 3
Neutropenia | 55 | 49 | 39 | 36
Leukopenia | 15 | 12 | 6 | 3
Febrile neutropenia | 10 | 10 | 8 | 8
Bronchitis | 6 | 1 | 4 | <1
a Includes events which occurred on the day of an infusion or within 24 hours of the end of an infusion and resulted in an interruption or discontinuation of treatment. Infusion reactions may include, but are not limited to, chills, dyspnea, flushing, hypotension, nausea, pain, pruritus, pyrexia, rash, and urticaria.

Adverse reactions associated with decreased platelet counts (including but not limited to thrombocytopenia, platelet count decreased and pancytopenia) and decreased hemoglobin (including but not limited to anemia, hemoglobin decreased and pancytopenia) occurred less frequently in the ARZERRA plus fludarabine and cyclophosphamide arm than in the fludarabine and cyclophosphamide arm up to 60 days after the last dose of study treatment: 30% (all grades) and 15% (Grade ≥3) vs 38% (all grades) and 28% (Grade ≥3), respectively for decreased platelet counts; and 23% (all grades) and 10% (Grade ≥3) vs 33% (all grades) and 16% (Grade ≥3), respectively for decreased hemoglobin.

Infusion Reactions: On Day 1 of infusion, infusion reactions occurred in 49% (7% were >Grade 3) of patients treated with ARZERRA plus fludarabine and cyclophosphamide, compared to 16% (1% were >Grade 3) of patients treated with fludarabine and cyclophosphamide and decreased with subsequent infusions. Infusion reactions led to discontinuation of treatment in 3% of patients in the ARZERRA plus fludarabine and cyclophosphamide. Serious adverse events of infusion reactions occurred in 2% of patients in the ARZERRA plus fludarabine and cyclophosphamide compared to <1% of patients treated with fludarabine and cyclophosphamide.

Neutropenia: The proportion of patients that had Grade 3 or greater neutropenia reported up to 60 days after the last dose of study medication was higher in patients treated with ARZERRA plus fludarabine and cyclophosphamide (51%) compared to the fludarabine and cyclophosphamide arm (37%). Grade 3 or greater neutropenic sepsis occurred in 2 patients (1%) treated with ARZERRA plus fludarabine and cyclophosphamide vs. 3 patients (2%) in the fludarabine and cyclophosphamide arm. Prolonged neutropenia occurred in 18 patients (10%) treated with ARZERRA plus fludarabine and cyclophosphamide vs. 20 patients (11%) in the fludarabine and cyclophosphamide arm. Late-onset neutropenia occurred in 13 patients (7%) treated with ARZERRA plus fludarabine and cyclophosphamide vs. 5 patients (3%) in the fludarabine and cyclophosphamide arm.

During the period between the first dose and 60 days after last dose there were five (3%) patients who died in the ARZERRA plus fludarabine and cyclophosphamide arm and ten (6%) patients who died in the fludarabine and cyclophosphamide arm.

Extended Treatment in CLL: The safety of ARZERRA was evaluated in an open-label, parallel-arm, randomized trial (Study 3) in 474 patients who had responded to therapy for their recurrent or progressive disease. Patients were randomized to receive ARZERRA as an intravenous infusion every 8 weeks or observation. The infusion schedule for ARZERRA was 300 mg on Day 1 followed 1 week later by 1,000 mg on Day 8 followed 7 weeks later by 1,000 mg and every 8 weeks thereafter for up to a maximum of 2 years. The data described in Table 7 include relevant adverse reactions occurring up to 60 days after the last dose of study medication (last visit for observation arm). The most common adverse reactions (≥10%) were infusion reactions, neutropenia, and upper respiratory tract infection (Table 7).

Table 7. Adverse Reactions with ≥5% Incidence in Patients Receiving ARZERRA and Also ≥2% More than in Patients in Observation Arm
 | ARZERRA (N = 237) |  | Observation Arm (N = 237)
Adverse Reactions | All Grades % | Grade ≥3 % | All Grades % | Grade ≥3 %
Infusion reactionsa | 46 | 4 | - | -
Neutropenia | 24 | 22 | 9 | 8
Upper respiratory tract infection | 19 | 1 | 9 | 0
Bronchitis | 9 | <1 | 7 | <1
Pneumonia | 8 | 5 | 5 | 3
Influenza | 6 | 0 | 3 | 0
Herpes zoster | 5 | <1 | 3 | <1
Insomnia | 5 | <1 | 2 | 0
Back pain | 5 | 0 | 3 | 0
Hypogammaglobulinemia | 5 | <1 | <1 | <1
a Includes events which occurred on the day of an infusion or within 24 hours of the end of an infusion and resulted in an interruption or discontinuation of treatment. Infusion reactions may include, but are not limited to, chills, dyspnea, flushing, hypotension, nausea, pain, pruritus, pyrexia, rash, and urticaria.

Infusion Reactions: Infusion reactions occurred in 25% of patients on the day of Infusion 1 (300 mg) and decreased with subsequent infusions (between 2% to 10%).

Infections: A total of 154 patients (65%) treated with ARZERRA compared with 120 patients (51%) in the observation arm experienced bacterial, viral, or fungal infections. The incidence of serious infections, however, was similar for patients treated with ARZERRA (20%) and the observation arm (18%). The proportions of fatal infections in patients treated with ARZERRA and in the observation arm were 2% and 3% respectively.

Neutropenia: The proportion of patients that had Grade 3 or greater neutropenia reported up to 60 days after the last dose of study medication was higher in patients treated with ARZERRA (22%) compared with the observation arm (8%). There were no cases of neutropenic sepsis reported with ARZERRA. Prolonged neutropenia occurred in 13 patients (5%) treated with ARZERRA and in 5 patients (2%) in the observation arm. Late-onset neutropenia occurred in 2 patients (<1%) treated with ARZERRA and 1 patient (<1%) in the observation arm.

During the period between the first dose and 60 days after last dose there were two (1%) patients in the ofatumumab group who died due to adverse events and five (2%) patients in the observation group.

Refractory CLL: The safety of monotherapy with ARZERRA was evaluated in 181 patients with relapsed or refractory CLL in 2 open-label, non-randomized, single-arm studies. In these studies, ARZERRA was administered at 2,000 mg beginning with the second dose for 11 doses (Study 4 [n = 154]) or 3 doses (Study 5 [n = 27]).

The data described in Table 8 and other sections below are derived from 154 patients in Study 4. All patients received 2,000 mg weekly from the second dose onward. Ninety percent (90%) of patients received at least 8 infusions of ARZERRA and 55% received all 12 infusions. The median age was 63 years (range: 41 to 86 years), 72% were male, and 97% were white.

In refractory CLL, the most common adverse reactions (≥10%) were neutropenia, pneumonia, pyrexia, cough, diarrhea, anemia, fatigue, dyspnea, rash, nausea, bronchitis, and upper respiratory tract infections (Table 8). The most common serious adverse reactions were infections (including pneumonia and sepsis), neutropenia, and pyrexia. Infections were the most common adverse reactions leading to drug discontinuation.

Table 8. Incidence of All Adverse Reactions Occurring in ≥5% of Patients and in the Fludarabine- and Alemtuzumab-refractory Subset
Adverse Reaction | Total Population; (N = 154) |  | Fludarabine‑ and Alemtuzumab‑refractory; (N = 59)
Adverse Reaction | All Grades; % | Grade ≥3; % | All Grades; % | Grade ≥3; %
Pneumoniaa | 23 | 14 | 25 | 15
Pyrexia | 20 | 3 | 25 | 5
Cough | 19 | 0 | 19 | 0
Diarrhea | 18 | 0 | 19 | 0
Anemia | 16 | 5 | 17 | 8
Fatigue | 15 | 0 | 15 | 0
Dyspnea | 14 | 2 | 19 | 5
Rashb | 14 | <1 | 17 | 2
Bronchitis | 11 | <1 | 19 | 2
Nausea | 11 | 0 | 12 | 0
Upper respiratory tract infection | 11 | 0 | 3 | 0
Edema peripheral | 9 | <1 | 8 | 2
Back pain | 8 | 1 | 12 | 2
Chills | 8 | 0 | 10 | 0
Nasopharyngitis | 8 | 0 | 8 | 0
Sepsisc | 8 | 8 | 10 | 10
Urticaria | 8 | 0 | 5 | 0
Insomnia | 7 | 0 | 10 | 0
Headache | 6 | 0 | 7 | 0
Herpes zoster | 6 | 1 | 7 | 2
Hyperhidrosis | 5 | 0 | 5 | 0
Hypertension | 5 | 0 | 8 | 0
Hypotension | 5 | 0 | 3 | 0
Muscle spasms | 5 | 0 | 3 | 0
Sinusitis | 5 | 2 | 3 | 2
Tachycardia | 5 | <1 | 7 | 2
a Includes pneumonia, lung infection, lobar pneumonia, and bronchopneumonia.
b Includes rash, rash macular, and rash vesicular.
c Includes sepsis, neutropenic sepsis, bacteremia, and septic shock.

Infusion Reactions: Infusion reactions occurred in 44% of patients on the day of the first infusion (300 mg), 29% on the day of the second infusion (2,000 mg), and less frequently during subsequent infusions.

Infections: A total of 108 patients (70%) experienced bacterial, viral, or fungal infections. A total of 45 patients (29%) experienced Grade 3 or greater infections, of which 19 (12%) were fatal. The proportion of fatal infections in the fludarabine‑ and alemtuzumab‑refractory group was 17%.

Neutropenia: Of 108 patients with normal neutrophil counts at baseline, 45 (42%) developed Grade 3 or greater neutropenia. Nineteen (18%) developed Grade 4 neutropenia. Some patients experienced new onset Grade 4 neutropenia >2 weeks in duration.

6.2 Immunogenicity

There is a potential for immunogenicity with therapeutic proteins such as ofatumumab. Serum samples from more than 926 patients with CLL were tested during and after treatment for antibodies to ARZERRA. Formation of anti-ofatumumab antibodies was observed in less than 1% of patients with CLL after treatment with ofatumumab.

Immunogenicity assay results are highly dependent on several factors including assay sensitivity and specificity, assay methodology, sample handling, timing of sample collection, concomitant medications, and underlying disease. For these reasons, comparison of incidence of antibodies to ARZERRA with the incidence of antibodies to other products may be misleading.

6.3 Postmarketing Experience

The following adverse reactions have been identified during post-approval use of ARZERRA. Because these reactions are reported voluntarily from a population of uncertain size, it is not always possible to reliably estimate their frequency or establish a causal relationship to drug exposure.

Infusion-related Cardiac Events

Cardiac arrest

Mucocutaneous Reactions

Stevens-Johnson syndrome, porphyria cutanea tarda

8 USE IN SPECIFIC POPULATIONS

8.1 Pregnancy

Risk Summary

ARZERRA may cause fetal B-cell depletion based on findings from animal studies and the drug’s mechanism of action [see Clinical Pharmacology (12.1)]. There are no data on ARZERRA use in pregnant women to inform a drug-associated risk. However, there are clinical considerations [see Clinical Considerations]. No teratogenicity was observed in animal reproduction studies with administration of ARZERRA to pregnant monkeys during organogenesis at doses 0.3 and 2.4 times the maximum recommended human dose (MRHD) of 2000 mg based on monkey geometric mean AUCinf of 213 mg.h/mL and 1646 mg.h/mL, respectively. However, ofatumumab caused depletion of maternal circulating B-cells, depletion of peripheral and splenic fetal B-cells, and decreased fetal spleen weights [see Data].

The estimated background risk of major birth defects and miscarriage for the indicated population is unknown. In the U.S. general population the estimated background risk of major birth defects is 2% to 4% and of miscarriage is 15% to 20% of clinically recognized pregnancies, respectively.

Clinical Considerations

Fetal/neonatal adverse reactions

ARZERRA may cause fetal B-cell depletion [see Data]. Avoid administering live vaccines to neonates and infants exposed to ARZERRA in utero until B-cell recovery occurs [see Warnings and Precautions (5.7) and Clinical Pharmacology (12.2)].

Data

Animal Data

In an embryo-fetal development study, pregnant cynomolgus monkeys received 20 or 100 mg/kg/day of ofatumumab intravenously (30 minute infusion) once weekly during the period of organogenesis [Gestation Days (GD) 20 to 50] with systemic exposure throughout pregnancy due to the long half-life as drug was detected in maternal serum on GD 100 (early fetal period of development). At the end of organogenesis on GD 48, the exposure in pregnant monkeys receiving ofatumumab 20 and 100 mg/kg/day was approximately 0.3 and 2.4 times the human exposure after the 8th infusion of the MRHD of 2,000 mg based on monkey geometric mean AUCinf of 213 mg.h/mL and 1,646 mg.h/mL, respectively. Ofatumumab crossed the placenta, as it was detected in fetal cord blood on GD 100 in both dose groups. There was no maternal toxicity and no effect on pregnancy success. As expected, both dose levels of ofatumumab depleted circulating B cells in the mothers; recovery of B lymphocytes in dosed animals was not observed during the dosing-free period. Following Caesarean section at GD 100, fetuses from treated mothers exhibited decreases in mean peripheral and splenic B-cell counts (decreased to approximately 12% and 15% of control values at both dose levels, respectively and spleen weights (decreased by approximately 15% in low-dose group and by approximately 30% in high-dose group, compared with control values). There was no effect on prenatal survival and no evidence of teratogenicity in this monkey study.

The kinetics of B-lymphocyte recovery and the potential long-term effects of perinatal B-cell depletion in offspring from ofatumumab-treated maternal monkeys have not been studied.

8.2 Lactation

Risk Summary

There is no information regarding the presence of ARZERRA in human milk, the effects on the breastfed infant, or the effects on milk production. Human IgG is known to be present in human milk. Published data suggest that antibodies in breast milk do not enter the neonatal and infant circulations in substantial amounts.

The developmental and health benefits of breastfeeding should be considered along with the mother’s clinical need for ARZERRA and any potential adverse effects on the breastfed infant from ARZERRA or from the underlying maternal condition.

8.4 Pediatric Use

Safety and effectiveness of ARZERRA have not been established in children.

8.5 Geriatric Use

In patients with previously untreated CLL (Study 1), 68% (148/217) receiving ARZERRA plus chlorambucil were 65 years and older. Patients age 65 years and older experienced a higher incidence of the following Grade 3 or greater adverse reactions compared with patients younger than 65 years of age: neutropenia (30% versus 17%) and pneumonia (5% versus 1%) [see Adverse Reactions (6.1)]. In patients 65 years and older, 29% experienced serious adverse events compared with 13% of patients younger than 65 years. No clinically meaningful differences in the effectiveness of ARZERRA plus chlorambucil were observed between older and younger patients [see Clinical Studies (14.1)].

In patients with relapsed CLL (Study 2), 33% (60/181) of patients receiving ARZERRA plus fludarabine and cyclophosphamide were 65 years and older. No clinically meaningful differences in the safety or effectiveness of ARZERRA were observed between patients age 65 years and older, and those younger than 65 years [see Adverse Reactions (6.1), Clinical Studies (14.2)].

With extended treatment in patients with CLL (Study 3), 49% (117/237) receiving ARZERRA were 65 years and older. No clinically meaningful differences in the safety or effectiveness of ARZERRA were observed between patients age 65 years and older and those younger than 65 years of age [see Adverse Reactions (6.1), Clinical Studies (14.3)].

In refractory CLL clinical studies there were insufficient numbers of patients aged 65 years and older to determine whether they respond differently from younger patients [see Clinical Pharmacology (12.3)].

11 DESCRIPTION

ARZERRA (ofatumumab) is an IgG1κ human monoclonal antibody with a molecular weight of approximately 149 kDa. The antibody was generated via transgenic mouse and hybridoma technology and is produced in a recombinant murine cell line (NS0) using standard mammalian cell cultivation and purification technologies.

ARZERRA is a sterile, clear to opalescent, colorless, preservative-free liquid concentrate for intravenous administration. ARZERRA is supplied at a concentration of 20 mg/mL in single-use vials. Each single-use vial contains either 100 mg ofatumumab in 5 mL of solution or 1,000 mg ofatumumab in 50 mL of solution.

Inactive ingredients include: 10 mg/mL arginine, diluted hydrochloric acid, 0.019 mg/mL edetate disodium, 0.2 mg/mL polysorbate 80, 6.8 mg/mL sodium acetate, 2.98 mg/mL sodium chloride, and Water for Injection, USP. The pH is 5.5.

12 CLINICAL PHARMACOLOGY

12.1 Mechanism of Action

Ofatumumab binds specifically to both the small and large extracellular loops of the CD20 molecule. The CD20 molecule is expressed on normal B lymphocytes (pre–B- to mature B-lymphocyte) and on B-cell CLL. The CD20 molecule is not shed from the cell surface and is not internalized following antibody binding.

The Fab domain of ofatumumab binds to the CD20 molecule and the Fc domain mediates immune effector functions to result in B-cell lysis in vitro. Data suggest that possible mechanisms of cell lysis include complement-dependent cytotoxicity and antibody-dependent, cell-mediated cytotoxicity.

12.2 Pharmacodynamics

B-cell Depletion: In patients with previously untreated CLL, at 6 months after the last dose, the median reductions in CD19-positive B cells were >99% (n = 155) for ARZERRA in combination with chlorambucil and 94% (n = 121) for chlorambucil alone.

In patients with relapsed CLL, the proportion of responders in the ofatumumab in combination with fludarabine and cyclophosphamide (O+FC) arm who showed complete or near complete B cell depletion was 39% (n = 59) and 82% (n = 126) , respectively. The proportion of responders in the fludarabine and cyclophosphamide (FC) arm with complete or near complete B cell depletion was 4% (n = 5) and 23% (n = 28), respectively.

In patients treated with extended treatment for CLL after response to therapy for their recurrent or progressive disease, the median decreases in B-cell counts were 61% (n = 168) after the first infusion and 80% (n = 114) prior to the sixth infusion; in the observation arm, the median changes in B-cell counts at the same time points were increases of 32% (n = 148) and 1,328% (n = 95).

In patients with CLL refractory to fludarabine and alemtuzumab, the median decrease in circulating CD19-positive B cells was 91% (n = 50) with the 8th infusion and 85% (n = 32) with the 12th infusion. The time to recovery of lymphocytes, including CD19-positive B cells, to normal levels has not been determined.

Although the depletion of B-cells in the peripheral blood is a measurable pharmacodynamic effect, it is not directly correlated with the depletion of B cells in solid organs or in malignant deposits. B-cell depletion has not been shown to be directly correlated to clinical response.

Cardiac Electrophysiology: The effect of multiple doses of ARZERRA on the QTc interval was evaluated in a pooled analysis of 3 open-label studies in patients with CLL (N = 85). Patients received ARZERRA 300 mg on Day 1 followed by either 1,000 mg or 2,000 mg for subsequent doses. No large changes in the mean QTc interval (i.e., >20 milliseconds) were detected in the pooled analysis.

12.3 Pharmacokinetics

Ofatumumab is eliminated through both a target-independent route and a B cell-mediated route. Ofatumumab exhibited dose-dependent clearance in the dose range of 100 to 2,000 mg. Due to the depletion of B cells, the clearance of ofatumumab decreased substantially after subsequent infusions compared with the first infusion.

Pharmacokinetic data were obtained after repeated administration (4, 5, 6, 8, or 12 infusions) of 1,000 mg or 2,000 mg doses in 774 patients with CLL (Studies 1, 2, 3, 4 and 5). The geometric mean (% CV) values for clearance, volume of distribution at steady state (Vss), and half-life for ofatumumab in these patients were 9.3 mL/hour (91%), 6.1 L (52%), and 17.6 days (83%). The pharmacokinetic profile was similar across doses in patients with CLL.

Specific Populations: The following population characteristics do not have a clinically meaningful effect on the pharmacokinetics of ofatumumab: body size, gender, age, and renal impairment (evaluated in patients with a calculated creatinine clearance ≥30 mL/min).

No formal studies of ARZERRA in patients with hepatic impairment have been conducted. The effect of a calculated CrCL < 30 mL/min on the pharmacokinetics of ARZERRA has not been evaluated.

Drug Interactions: Coadministration of ARZERRA did not result in clinically relevant effects on the pharmacokinetics of fludarabine, cyclophosphamide, chlorambucil, or its active metabolite, phenylacetic acid mustard.

13 NONCLINICAL TOXICOLOGY

13.1 Carcinogenesis, Mutagenesis, Impairment of Fertility

No carcinogenicity or mutagenicity studies of ofatumumab have been conducted. In a repeat-dose toxicity study, no tumorigenic or unexpected mitogenic responses were noted in cynomolgus monkeys treated for 7 months with up to 3.5 times the maximum human dose (2,000 mg) of ofatumumab. Effects on male and female fertility have not been evaluated in animal studies.

14 CLINICAL STUDIES

14.1 Previously Untreated CLL

The efficacy of ARZERRA was evaluated in a randomized, open-label, parallel-arm study; 447 patients previously untreated for CLL were randomized to receive either ARZERRA as monthly intravenous infusions (Cycle 1: 300 mg on Day 1 and 1,000 mg on Day 8; subsequent cycles: 1,000 mg on Day 1 every 28 days) in combination with chlorambucil (10 mg/m2 orally on Days 1 to 7 every 28 days) or chlorambucil alone (10 mg/m2 orally on Days 1 to 7 every 28 days). Patients received treatment for a minimum of 3 cycles. Treatment was continued for 3 cycles beyond maximal response (2 consecutive response assessments of stable disease, partial response, or complete response) for up to 12 cycles. Approximately 60% of patients received 3 to 6 cycles of ARZERRA and 30% received 7 to 12 cycles.

This trial enrolled patients for whom fludarabine-based therapy was considered to be inappropriate by the investigator for reasons that included advanced age or presence of co-morbidities. In the overall trial population, the median age was 69 years (range: 35 to 92 years) and 69% of patients in both arms were at least 65 years of age. In the overall trial population, 72% of patients had 2 or more co-morbidities and 48% of patients had a creatinine clearance of less than 70 mL/min. Sixty-three percent (63%) of patients were male and 89% were white. Elevated beta-2 microglobulin (β2m) >3,500 mcg/L was present in 72% of patients at baseline.

Efficacy was evaluated by progression-free-survival (PFS) as assessed by a blinded Independent Review Committee (IRC) using the International Workshop for Chronic Lymphocytic Leukemia (IWCLL) updated National Cancer Institute-sponsored Working Group (NCI-WG) guidelines (2008). ARZERRA plus chlorambucil resulted in statistically significant improvement in IRC-assessed median PFS compared with chlorambucil alone (22.4 months versus 13.1 months; hazard ratio: 0.57 [0.45, 0.72]) (Table 9; Figure 1).

Secondary efficacy endpoints, including overall response (OR), complete response (CR), and duration of response, were also assessed by the IRC using the 2008 IWCLL Guidelines (Table 9).

Table 9. IRC-assessed Efficacy Results in Previously Untreated CLL (ITT Populationa)
Primary and Key Secondary Endpoints | ARZERRA plus Chlorambucil; (N = 221) | Chlorambucil; (N = 226)
Progression-free survival (PFS); Median, months (95% CI) | 22.4; (19.0, 25.2) | 13.1; (10.6, 13.8)
Hazard ratiob (95% CI); Stratified log rank P value | 0.57 (0.45, 0.72); P <0.001
Overall response, % (95% CI) | 82.4; (76.7, 87.1) | 68.6; (62.1, 74.6)
P value | P = 0.001
Complete response, % | 12 | 1
Duration of response Median, months (95% CI) | 22.1; (19.1, 24.6) | 13.2; (10.8, 16.4)
IRC = Independent Review Committee; ITT = Intention to treat; CI = Confidence interval.
a Intention-to-treat population includes all 447 randomized patients.
b Pike Estimator.

Figure 1. Kaplan-Meier Estimates of IRC-assessed Progression-free Survival

14.2 Relapsed CLL

Study 2 (randomized, open-label, parallel-arm, multicenter trial) evaluated the efficacy of ARZERRA in combination with fludarabine and cyclophosphamide compared with fludarabine and cyclophosphamide in 365 patients with relapsed CLL. Baseline disease characteristics and prognostic markers were balanced between treatment arms. Patient median age was 61 years (range: 32 to 90 years), 60% were male and 55% and 28% of patients were Binet stage B and C, respectively. Eighty one percent (81%) of patients received 1-2 prior treatments and 21% of patients had received prior rituximab.

Patients received ARZERRA as intravenous infusions (Cycle 1: 300 mg on Day 1 and 1,000 mg on Day 8; followed by 1,000 mg on Day 1 of subsequent cycles). Approximately 90% of patients received 3-6 cycles of ARZERRA and 66% completed all 6 cycles.

Efficacy was evaluated by progression-free survival (PFS), as assessed by an independent review committee (IRC). PFS was prolonged in the ARZERRA plus fludarabine and cyclophosphamide (O+FC) arm compared to the fludarabine and cyclophosphamide (FC) arm (Table 10) resulting in a 10 months improvement in median PFS (mPFS) (see Figure 2).

Table 10. IRC-assessed Efficacy Results in relapsed CLL (ITT Population)
Primary and Key Secondary Endpoints | ARZERRA plus Fludarabine and Cyclophosphamide; (N = 183) | Fludarabine and Cyclophosphamide; (N = 182)
Progression-free survival (PFS); Median, months (95% CI)a | 28.9 (22.8, 35.9) | 18.8 (14.4, 25.8)
Hazard ratiob (95% CI); Stratified log rank P value | 0.67 (0.51, 0.88); P = 0.0032
Overall response, % (95% CI) | 84 (77, 89) | 68 (60, 74)
P valuec | P = 0.0003
Complete response | 27% | 7%
Complete response with incomplete bone marrow recovery | 2% | 1%
a Confidence intervals were obtained using the Brookmeyer-Crowley method.
b Hazard ratios were obtained using the Pike estimator. A hazard ratio<1 indicates a lower risk with O+FC compared with FC. The hazard ratio and p-value from the stratified log-rank test are adjusted for Binet stage and number of prior therapies.
c Cochran-Mantel-Haenzel test, adjusting for stratification factors: Binet stage and number of prior therapies.

Figure 2. Kaplan-Meier Estimates of IRC-assessed Progression-free Survival

With a median follow-up of approximately 34 months, overall survival results showed a HR of 0.78 [95% CI: 0.56-1.09]. The median overall survival was 56.4 months [95% CI: 44.2, NC] in the O+FC arm and was 45.8 months [95% CI: 37.3, NC] in the FC arm.

14.3 Extended Treatment in CLL

The efficacy of ARZERRA as extended treatment in CLL was evaluated in a randomized, parallel arm, open-label trial. In this trial, 474 patients who were in complete or partial response after at least two lines of prior therapy, were randomized to receive ARZERRA as intravenous infusions (300 mg on Day 1 followed 1 week later by 1,000 mg on Day 8 followed 7 weeks later by 1,000 mg and every 8 weeks thereafter for up to a maximum of 2 years) or observation.

In the overall trial population, the median age was 65 years (range: 33 to 87 years), 68% were male, and 96% were white. Most patients were in partial remission (81%), had two prior treatments (70%), and had received chemoimmunotherapy (80%) as prior therapy. The main efficacy outcome was progression-free survival (PFS) as assessed by the investigator.

At the time of the efficacy analysis, the median follow-up was 19.4 months with the ARZERRA arm and 18.7 months with the observation arm. The event rate (progressed or died) was 33% in the ARZERRA arm and 51% in the observation arm. The investigator-assessed median PFS was 29.4 months in the ARZERRA arm and 15.2 months in the observation arm (hazard ratio: 0.50 with 95% confidence interval [0.38, 0.66]; P <0.0001).

Figure 3. Kaplan-Meier Estimates of Investigator-assessed Progression-free Survival

14.4 Refractory CLL

Study 4 was a single-arm, multicenter trial in 154 patients with relapsed or refractory CLL. ARZERRA was administered by intravenous infusion according to the following schedule: 300 mg (Week 0), 2,000 mg weekly for 7 infusions (Weeks 1 through 7), and 2,000 mg every 4 weeks for 4 infusions (Weeks 12 through 24). Patients with CLL refractory to fludarabine and alemtuzumab (n = 59) comprised the efficacy population. Drug refractoriness was defined as failure to achieve at least a partial response to, or disease progression within 6 months of, the last dose of fludarabine or alemtuzumab. The main efficacy outcome was durable objective tumor response rate. Objective tumor responses were determined using the 1996 NCI-WG Guidelines for CLL.

In patients with CLL refractory to fludarabine and alemtuzumab, the median age was 64 years (range: 41 to 86 years), 75% were male, and 95% were white. The median number of prior therapies was 5; 93% received prior alkylating agents, 59% received prior rituximab, and all received prior fludarabine and alemtuzumab. Eighty-eight percent of patients received at least 8 infusions of ARZERRA and 54% received 12 infusions.

The investigator-determined overall response rate in patients with CLL refractory to fludarabine and alemtuzumab was 42% (99% CI: 26, 60) with a median duration of response of 6.5 months (95% CI: 5.8, 8.3). There were no complete responses. Anti-tumor activity was also observed in additional patients in Study 4 and in a multicenter, open-label, dose-escalation study (Study 5) conducted in patients with relapsed or refractory CLL.

16 HOW SUPPLIED/STORAGE AND HANDLING

ARZERRA (ofatumumab) is a sterile, clear to opalescent, colorless, preservative-free liquid concentrate (20 mg/mL) for dilution and intravenous administration provided in single-use glass vials with a rubber stopper (not made with natural rubber latex) and an aluminum overseal. Each vial contains either 100 mg ofatumumab in 5 mL of solution or 1,000 mg ofatumumab in 50 mL of solution.

ARZERRA is available as follows:

Carton Contents | NDC
3 single-use 100 mg/5 mL vials | Vial: NDC 0078-0669-61; Carton of 3 vials: NDC 0078-0669-13
1 single-use 1,000 mg/50 mL vial | Vial and Carton: NDC 0078-0690-61

STORAGE AND HANDLING

Store ARZERRA refrigerated between 2° to 8°C (36° to 46°F). Do not freeze. Vials should be protected from light.

17 PATIENT COUNSELING INFORMATION

Advise patients to contact a healthcare professional for any of the following:

- Signs and symptoms of infusion reactions including fever, chills, rash, or breathing problems within 24 hours of infusion [see Warnings and Precautions (5.1), Adverse Reactions (6.1)]
- Symptoms of hepatitis including worsening fatigue or yellow discoloration of skin or eyes [see Warnings and Precautions (5.2, 5.3)]
- New neurological symptoms such as confusion, dizziness or loss of balance, difficulty talking or walking, or vision problems [see Warnings and Precautions (5.4)]
- Bleeding, easy bruising, petechiae, pallor, worsening weakness, or fatigue [see Warnings and Precautions (5.6)]
- Signs of infections including fever and cough [see Warnings and Precautions (5.6), Adverse Reactions (6.1)]
- Pregnancy- Advise pregnant women of potential fetal B-cell depletion [see Use in Specific Populations (8.1, 8.2)]

Advise patients of the need for:

- Monitoring and possible need for treatment if they have a history of hepatitis B infection (based on the blood test) [see Warnings and Precautions (5.2)].
- Periodic monitoring for blood counts [see Warnings and Precautions (5.6)]
- Avoiding vaccination with live viral vaccines [see Warnings and Precautions (5.7)]

Manufactured by:
Novartis Pharmaceuticals Corporation
East Hanover, New Jersey 07936
US License 1244
At
Glaxo Group Ltd
Brentford, Middlesex, UK

© Novartis

T2016-73
August 2016

PACKAGE LABEL

Principal Display Panel

NDC 0078-0669-13

Arzerra®

(ofatumumab)

Injection, for Intravenous Infusion

100 mg/5 mL(20mg/mL)

Rx only

For Intravenous Infusion Only.

Must Be Diluted Prior To Administration.

Contains 3 vials

Single-Use Vials - Discard Unused Portion

Novartis

PACKAGE LABEL

Principal Display Panel

NDC 0078-0690-61

Arzerra®

(ofatumumab)

Injection, for Intravenous Infusion

1000 mg/50 mL(20mg/mL)

Rx only

For Intravenous Infusion Only.

Must Be Diluted Prior To Administration.

Contains 1 vial

Single-Use Vials - Discard Unused Portion

Novartis